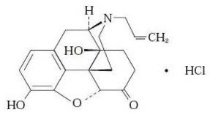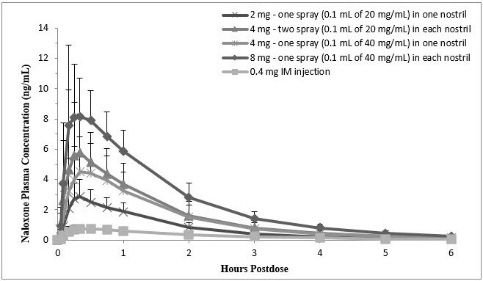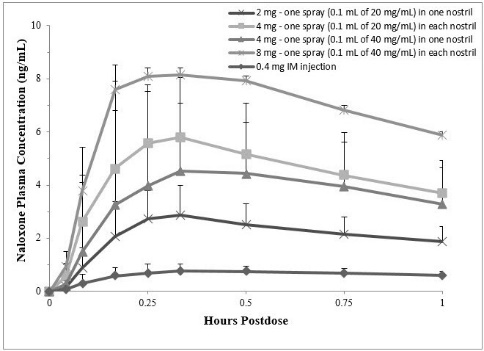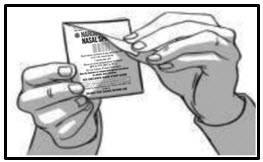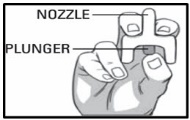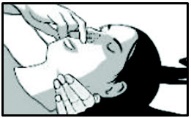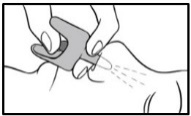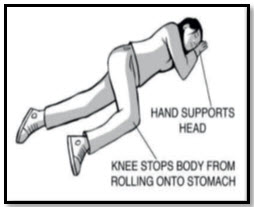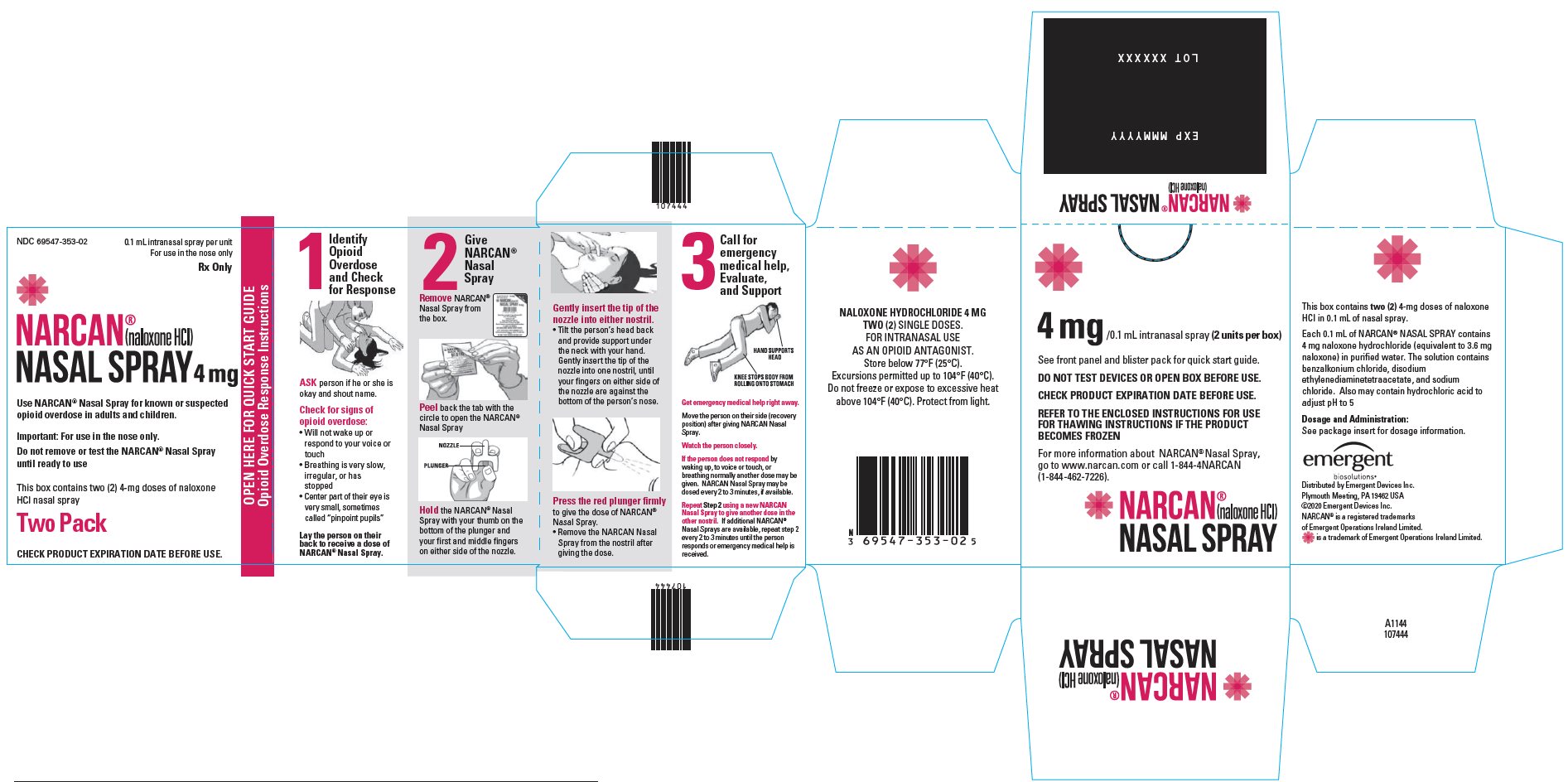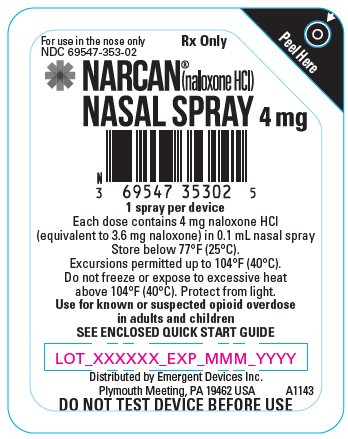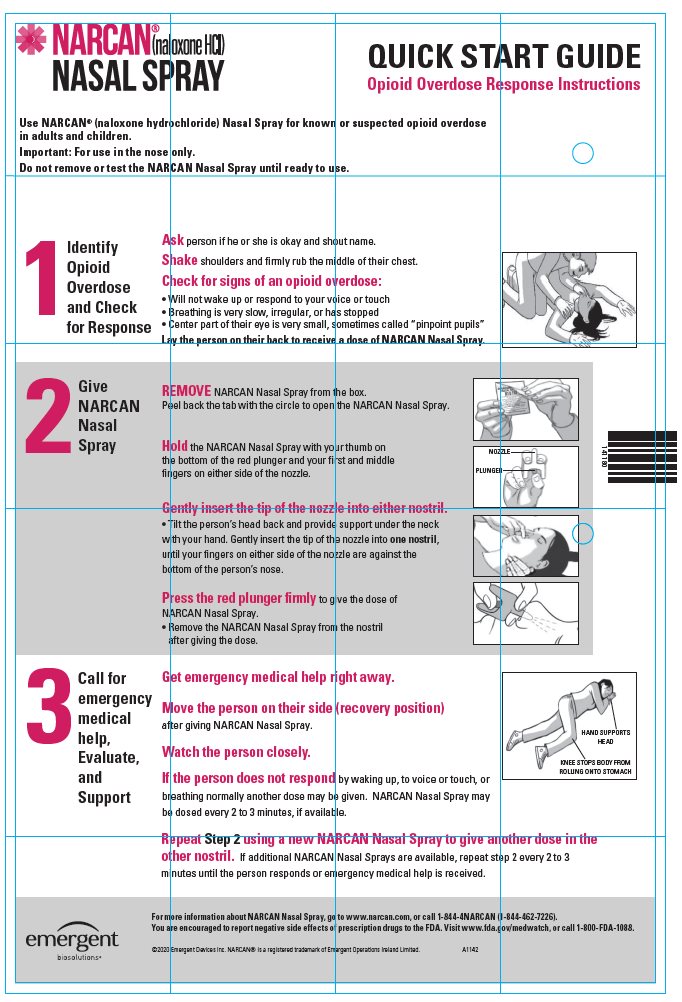 DRUG LABEL: Narcan
NDC: 69547-353 | Form: SPRAY
Manufacturer: Emergent Devices Inc.
Category: prescription | Type: HUMAN PRESCRIPTION DRUG LABEL
Date: 20251205

ACTIVE INGREDIENTS: NALOXONE HYDROCHLORIDE 4 mg/0.1 mL
INACTIVE INGREDIENTS: BENZALKONIUM CHLORIDE; EDETATE DISODIUM; SODIUM CHLORIDE; WATER; HYDROCHLORIC ACID

HIGHLIGHTS OF PRESCRIBING INFORMATION

These highlights do not include all the information needed to use NARCAN®NASAL SPRAY safely and effectively. See full prescribing information for NARCAN®NASAL SPRAY.
NARCAN®(naloxone hydrochloride) nasal spray
Initial U.S. Approval: 1971

1 INDICATIONS AND USAGE

NARCAN Nasal Spray is an opioid antagonist indicated for the emergency treatment of known or suspected opioid overdose, as manifested by respiratory and/or central nervous system depression. (1)

NARCAN Nasal Spray is intended for immediate administration as emergency therapy in settings where opioids may be present. (1)

NARCAN Nasal Spray is not a substitute for emergency medical care. (1)

2 DOSAGE AND ADMINISTRATION

- NARCAN Nasal Spray is for intranasal use only. (2.1)
- Seek emergency medical care immediately after use. (2.1)
- Administration of a single spray of NARCAN Nasal Spray intranasally into one nostril. (2.2)
- Administer additional doses of NARCAN Nasal Spray, using a new nasal spray with each dose, if the patient does not respond or responds and then relapses into respiratory depression, additional doses of NARCAN Nasal Spray may be given every 2 to 3 minutes until emergency medical assistance arrives. (2.2)
- Additional supportive and/or resuscitative measures may be helpful while awaiting emergency medical assistance. (2.2)

3 DOSAGE FORMS AND STRENGTHS

Nasal spray 4 mg of naloxone hydrochloride in 0.1 mL. (3)

4 CONTRAINDICATIONS

Hypersensitivity to naloxone hydrochloride. (4)

5 WARNINGS AND PRECAUTIONS

- Risk of Recurrent Respiratory and CNS Depression: Due to the duration of action of naloxone relative to the opioid, keep patient under continued surveillance and administer repeat doses of naloxone using a new nasal spray with each dose, as necessary, while awaiting emergency medical assistance. (5.1)
- Risk of Limited Efficacy with Partial Agonists or Mixed Agonists/Antagonists: Reversal of respiratory depression caused by partial agonists or mixed agonists/antagonists, such as buprenorphine and pentazocine, may be incomplete. Larger or repeat doses may be required. (5.2)
- Precipitation of Severe Opioid Withdrawal: Use in patients who are opioid dependent may precipitate opioid withdrawal. In neonates, opioid withdrawal may be life-threatening if not recognized and properly treated. Monitor for the development of opioid withdrawal. (5.3)
- Risk of Cardiovascular (CV) Effects:Abrupt postoperative reversal of opioid depression may result in adverse CV effects. These events have primarily occurred in patients who had pre-existing CV disorders or received other drugs that may have similar adverse CV effects. Monitor these patients closely in an appropriate healthcare setting after use of naloxone hydrochloride. (5.3)

6 ADVERSE REACTIONS

The following adverse reactions were observed in a NARCAN Nasal Spray clinical study: increased blood pressure, constipation, toothache, muscle spasms, musculoskeletal pain, headache, nasal dryness, nasal edema, nasal congestion, nasal inflammation, rhinalgia, and xeroderma. (6)

To report SUSPECTED ADVERSE REACTIONS, contact Emergent Devices Inc. at 1-844-4NARCAN (1-844-462-7226) or FDA at 1-800-FDA-1088 or www.fda.gov/medwatch.

FULL PRESCRIBING INFORMATION

1 INDICATIONS AND USAGE

NARCAN Nasal Spray is indicated for the emergency treatment of known or suspected opioid overdose, as manifested by respiratory and/or central nervous system depression.

NARCAN Nasal Spray is intended for immediate administration as emergency therapy in settings where opioids may be present.

NARCAN Nasal Spray is not a substitute for emergency medical care.

2 DOSAGE AND ADMINISTRATION

2.1 Important Administration Instructions

NARCAN Nasal Spray is for intranasal use only.

No additional device assembly is required.

Because treatment of suspected opioid overdose must be performed by someone other than the patient, instruct the prescription recipient to inform those around them about the presence of NARCAN Nasal Spray and the Instructions for Use.

Instruct the patient or caregiver to read the Instructions for Useat the time they receive a prescription for NARCAN Nasal Spray. Emphasize the following instructions to the patient or caregiver:

- Administer NARCAN Nasal Spray as quickly as possible because prolonged respiratory depression may result in damage to the central nervous system or death. Since the duration of action of most opioids exceeds that of naloxone hydrochloride and the suspected opioid overdose may occur outside of supervised medical settings, seek immediate emergency medical assistance, keep the patient under continued surveillance until emergency personnel arrive, and administer repeated doses of NARCAN Nasal Spray, as necessary. Always seek emergency medical assistance in the event of a suspected, potentially life-threatening opioid emergency after administration of the first dose of NARCAN Nasal Spray.
- Additional doses of NARCAN Nasal Spray may be required until emergency medical assistance becomes available.
- Do not attempt to reuse NARCAN Nasal Spray. Each NARCAN Nasal Spray contains a single dose of naloxone and cannot be reused.
- Re-administer NARCAN Nasal Spray, using a new nasal spray, every 2 to 3 minutes if the patient does not respond or responds and then relapses into respiratory depression.
- Administer NARCAN Nasal Spray in alternate nostrils with each dose.
- Administer NARCAN Nasal Spray according to the printed instructions on the device label and the Instructions for Use.
- Place the patient in the supine position. Prior to administration, be sure the device nozzle is inserted in either nostril of the patient, and provide support to the back of the neck to allow the head to tilt back. Do not prime or test the device prior to administration.
- To administer the dose press firmly on the device plunger.
- Remove the device nozzle from the nostril after use.
- Turn patient on their side as shown in the Instructions for Useand call for emergency medical assistance immediately after administration of the first dose of NARCAN Nasal Spray.

2.2 Dosing in Adults and Pediatric Patients

Initial Dosing

The recommended initial dose of NARCAN Nasal Spray in adults and pediatric patients is one spray delivered by intranasal administration into one nostril.

Repeat Dosing

Seek emergency medical assistance as soon as possible after administering the first dose of NARCAN Nasal Spray.

The requirement for repeat doses of NARCAN Nasal Spray depends upon the amount, type, and route of administration of the opioid being antagonized.

Administer NARCAN Nasal Spray in alternate nostrils with each dose.

If the patient responds to NARCAN Nasal Spray and relapses back into respiratory depression before emergency assistance arrives, administer an additional dose of NARCAN Nasal Spray using a new NARCAN Nasal Spray and continue surveillance of the patient.

If the desired response is not obtained after 2 or 3 minutes, administer an additional dose of NARCAN Nasal Spray using a new NARCAN Nasal Spray. If there is still no response and additional doses are available, administer additional doses of NARCAN Nasal Spray every 2 to 3 minutes using a new NARCAN Nasal Spray with each dose until emergency medical assistance arrives.

Additional supportive and/or resuscitative measures may be helpful while awaiting emergency medical assistance.

2.3 Dosing Modifications due to Partial Agonists or Mixed Agonist/Antagonists

Reversal of respiratory depression by partial agonists or mixed agonist/antagonists, such as buprenorphine and pentazocine, may be incomplete and require higher doses of naloxone hydrochloride or repeated administration of NARCAN Nasal Spray using a new nasal spray [see Warnings and Precautions (5.2)] .

3 DOSAGE FORMS AND STRENGTHS

NARCAN Nasal Spray is supplied as a single-dose intranasal spray containing 4 mg of naloxone hydrochloride in 0.1 mL.

4 CONTRAINDICATIONS

NARCAN Nasal Spray is contraindicated in patients known to be hypersensitive to naloxone hydrochloride or to any of the other ingredients.

5 WARNINGS AND PRECAUTIONS

5.1 Risk of Recurrent Respiratory and Central Nervous System Depression

The duration of action of most opioids may exceed that of NARCAN Nasal Spray resulting in a return of respiratory and/or central nervous system depression after an initial improvement in symptoms. Therefore, it is necessary to seek emergency medical assistance immediately after administration of the first dose of NARCAN Nasal Spray and to keep the patient under continued surveillance. Administer additional doses of NARCAN Nasal Spray if the patient is not adequately responding or responds and then relapses back into respiratory depression, as necessary [see Dosage and Administration (2.2)] . Additional supportive and/or resuscitative measures may be helpful while awaiting emergency medical assistance.

5.2 Risk of Limited Efficacy with Partial Agonists or Mixed Agonist/Antagonists

Reversal of respiratory depression by partial agonists or mixed agonist/antagonists such as buprenorphine and pentazocine, may be incomplete. Larger or repeat doses of naloxone hydrochloride may be required to antagonize buprenorphine because the latter has a long duration of action due to its slow rate of binding and subsequent slow dissociation from the opioid receptor [see Dosage and Administration (2.3)] . Buprenorphine antagonism is characterized by a gradual onset of the reversal effects and a decreased duration of action of the normally prolonged respiratory depression.

5.3 Precipitation of Severe Opioid Withdrawal

The use of NARCAN Nasal Spray in patients who are opioid-dependent may precipitate opioid withdrawal characterized by the following signs and symptoms: body aches, diarrhea, tachycardia, fever, runny nose, sneezing, piloerection, sweating, yawning, nausea or vomiting, nervousness, restlessness or irritability, shivering or trembling, abdominal cramps, weakness, and increased blood pressure. In neonates, opioid withdrawal may be life-threatening if not recognized and properly treated and may include the following signs and symptoms: convulsions, excessive crying, and hyperactive reflexes .Monitor the patient for the development of the signs and symptoms of opioid withdrawal.

Abrupt postoperative reversal of opioid depression after using naloxone hydrochloride may result in nausea, vomiting, sweating, tremulousness, tachycardia, hypotension, hypertension, seizures, ventricular tachycardia and fibrillation, pulmonary edema, and cardiac arrest. Death, coma, and encephalopathy have been reported as sequelae of these events. These events have primarily occurred in patients who had pre-existing cardiovascular disorders or received other drugs that may have similar adverse cardiovascular effects. Although a direct cause and effect relationship has not been established, after use of naloxone hydrochloride, monitor patients with pre-existing cardiac disease or patients who have received medications with potential adverse cardiovascular effects for hypotension, ventricular tachycardia or fibrillation, and pulmonary edema in an appropriate healthcare setting. It has been suggested that the pathogenesis of pulmonary edema associated with the use of naloxone hydrochloride is similar to neurogenic pulmonary edema, i.e., a centrally mediated massive catecholamine response leading to a dramatic shift of blood volume into the pulmonary vascular bed resulting in increased hydrostatic pressures.

There may be clinical settings, particularly the postpartum period in neonates with known or suspected exposure to maternal opioid use, where it is preferable to avoid the abrupt precipitation of opioid withdrawal symptoms. In these settings, consider use of an alternative, naloxone-containing product that can be titrated to effect and, where applicable, dosed according to weight. [see Use in Specific Populations (8.4)] .

6 ADVERSE REACTIONS

The following serious adverse reactions are discussed elsewhere in the labeling:

- Precipitation of Severe Opioid Withdrawal [see Warnings and Precautions (5.3)]

Because clinical studies are conducted under widely varying conditions, adverse reaction rates observed in the clinical studies of a drug cannot be directly compared to the rates in the clinical studies of another drug and may not reflect the rates observed in practice.

The following adverse reactions were observed in a NARCAN Nasal Spray clinical study.

In a pharmacokinetic study of 30 healthy adult volunteers exposed to one spray of NARCAN Nasal Spray in one nostril or two sprays of NARCAN Nasal Spray, one in each nostril, the most common adverse reactions were: increased blood pressure, constipation, toothache, muscle spasms, musculoskeletal pain, headache, nasal dryness, nasal edema, nasal congestion, nasal inflammation, rhinalgia, and xeroderma.

The following adverse reactions have been identified primarily during post-approval use of naloxone hydrochloride in the post-operative setting. Because these reactions are reported voluntarily from a population of uncertain size, it is not always possible to reliably estimate their frequency or establish a causal relationship to drug exposure: Hypotension, hypertension, ventricular tachycardia and fibrillation, dyspnea, pulmonary edema, and cardiac arrest. Death, coma, and encephalopathy have been reported as sequelae of these events. Excessive doses of naloxone hydrochloride in post-operative patients have resulted in significant reversal of analgesia, and have caused agitation.

Abrupt reversal of opioid effects in persons who were physically dependent on opioids has precipitated an acute withdrawal syndrome. Signs and symptoms have included: body aches, fever, sweating, runny nose, sneezing, piloerection, yawning, weakness, shivering or trembling, nervousness, restlessness or irritability, diarrhea, nausea or vomiting, abdominal cramps, increased blood pressure, tachycardia. In some patients, there may be aggressive behavior upon abrupt reversal of an opioid overdose. In the neonate, opioid withdrawal signs and symptoms also included convulsions, excessive crying, and hyperactive reflexes.

8 USE IN SPECIFIC POPULATIONS

8.1 Pregnancy

Risk Summary

The limited available data on naloxone use in pregnant women are not sufficient to inform a drug-associated risk. However, there are clinical considerations [see Clinical Considerations] . In animal reproduction studies, no embryotoxic or teratogenic effects were observed in mice and rats treated with naloxone hydrochloride during the period of organogenesis at doses equivalent to 6-times and 12-times, respectively, a human dose of 8 mg/day (two NARCAN Nasal Sprays) based on body surface area comparison [see Data] .

The estimated background risk of major birth defects and miscarriage for the indicated population is unknown. In the U.S. general population, the estimated background risk of major birth defects and miscarriage in clinically recognized pregnancies is 2% to 4% and 15% to 20%, respectively.

Clinical Considerations

Fetal/Neonatal adverse reactions

Naloxone hydrochloride crosses the placenta, and may precipitate withdrawal in the fetus, as well as in the opioid-dependent mother [see Warnings and Precautions (5.3)] . The fetus should be evaluated for signs of distress after NARCAN Nasal Spray is used. Careful monitoring is needed until the fetus and mother are stabilized.

Data

Animal Data

Naloxone hydrochloride was administered during organogenesis to mice and rats at subcutaneous doses up to 10 mg/kg/day (equivalent to 6-times and 12-times, respectively, a human dose of 8 mg (two NARCAN Nasal Sprays)) (based on body surface area comparison). These studies demonstrated no embryotoxic or teratogenic effects due to naloxone hydrochloride.

Pregnant female rats were administered 2 or 10 mg/kg naloxone subcutaneously from Gestation Day 15 to Postnatal day 21. There were no adverse effects on the offspring (up to 12-times a human dose of 8 mg/day (two NARCAN Nasal Sprays) based on body surface area comparison).

8.2 Lactation

Risk Summary

There is no information regarding the presence of naloxone in human milk, or the effects of naloxone on the breastfed infant or on milk production. Studies in nursing mothers have shown that naloxone does not affect prolactin or oxytocin hormone levels. Naloxone is minimally orally bioavailable.

8.4 Pediatric Use

The safety and effectiveness of NARCAN Nasal Spray have been established in pediatric patients of all ages for known or suspected opioid overdose as manifested by respiratory and/or central nervous system depression. Use of naloxone hydrochloride in all pediatric patients is supported by adult bioequivalence studies coupled with evidence from the safe and effective use of other naloxone hydrochloride drug products. No pediatric studies were conducted for NARCAN Nasal Spray.

Absorption of naloxone hydrochloride following intranasal administration in pediatric patients may be erratic or delayed. Even when the opiate-intoxicated pediatric patient responds appropriately to naloxone hydrochloride, he/she must be carefully monitored for at least 24 hours, as a relapse may occur as naloxone hydrochloride is metabolized.

In opioid-dependent pediatric patients, (including neonates), administration of naloxone hydrochloride may result in an abrupt and complete reversal of opioid effects, precipitating an acute opioid withdrawal syndrome. Neonatal opioid withdrawal syndrome, unlike opioid withdrawal syndrome in adults, may be life-threatening, if not recognized, and should be treated according to protocols developed by neonatology experts [see Warnings and Precautions (5.3)] .

In settings such as in neonates with known or suspected exposure to maternal opioid use, where it may be preferable to avoid the abrupt precipitation of opioid withdrawal symptoms, consider use of an alternate naloxone-containing product that can be dosed according to weight and titrated to effect.

Also, in situations where the primary concern is for infants at risk for opioid overdose, consider whether the availability of alternate naloxone-containing products may be better suited than NARCAN Nasal Spray.

8.5 Geriatric Use

Geriatric patients have a greater frequency of decreased hepatic, renal, or cardiac function and of concomitant disease or other drug therapy. Therefore, the systemic exposure of naloxone hydrochloride can be higher in these patients.

Clinical studies of naloxone hydrochloride did not include sufficient numbers of subjects aged 65 and over to determine whether they respond differently from younger subjects. Other reported clinical experience has not identified differences in responses between the elderly and younger patients.

11 DESCRIPTION

NARCAN (naloxone hydrochloride) Nasal Spray is a pre-filled, single dose intranasal spray. Chemically, naloxone hydrochloride is the hydrochloride salt of 17-Allyl-4,5α-epoxy-3,14-dihydroxymorphinan-6-one hydrochloride with the following structure:

C19H21NO4∙ HCl

M.W. 363.84

Naloxone hydrochloride, an opioid antagonist, occurs as a white to slightly off-white powder, and is soluble in water, in dilute acids, and in strong alkali; slightly soluble in alcohol; practically insoluble in ether and in chloroform.

Each NARCAN Nasal Spray contains a 4 mg single dose of naloxone hydrochloride (equivalent to 3.6 mg of Naloxone) in a 0.1 mL (100 microliter) aqueous solution.

Inactive ingredients include benzalkonium chloride (preservative), disodium ethylenediaminetetraacetate (stabilizer), sodium chloride, hydrochloric acid to adjust pH, and purified water. The pH range is 3.5 to 5.5.

12 CLINICAL PHARMACOLOGY

12.1 Mechanism of Action

Naloxone hydrochloride is an opioid antagonist that antagonizes opioid effects by competing for the same receptor sites.

Naloxone hydrochloride reverses the effects of opioids, including respiratory depression, sedation, and hypotension. It can also reverse the psychotomimetic and dysphoric effects of agonist-antagonists such as pentazocine.

12.2 Pharmacodynamics

When naloxone hydrochloride is administered intravenously, the onset of action is generally apparent within two minutes. The time to onset of action is shorter for intravenous compared to subcutaneous or intramuscular routes of administration. The duration of action is dependent upon the dose and route of administration of naloxone hydrochloride.

12.3 Pharmacokinetics

In a pharmacokinetic study in 30 healthy adult subjects, the relative bioavailability (BA) of one nasal spray in one nostril, consisting of a 2 mg total dose (0.1 mL of 20 mg/mL naloxone hydrochloride solution) and a 4 mg total dose (0.1 mL of 40 mg/mL naloxone hydrochloride solution), and two nasal sprays administered as one nasal spray in each nostril, consisting of a 4 mg total dose (0.1 mL of 20 mg/mL naloxone hydrochloride solution in each nostril) and an 8 mg total dose (0.1 mL of 40 mg/mL naloxone hydrochloride solution in each nostril), were compared to a single dose of 0.4 mg naloxone hydrochloride intramuscular injection. For intranasal administration, the subjects were instructed not to breathe through the nose during administration of the nasal spray, and remained fully supine for approximately one hour post-dose. For intramuscular administration, naloxone was administered as a single injection in the gluteus maximus muscle. The pharmacokinetic parameters obtained in the study are shown in Table 1.

Table 1 Mean Pharmacokinetic Parameters (CV%) for Naloxone Following NARCAN (Naloxone HCl) Nasal Spray and Intramuscular Injection of Naloxone HCl to Healthy Subjects
Parameter | 2 mg – One Nasal Spray in one nostril 20 mg/ml (N=29) | 4 mg – Two Nasal Sprays, one in each nostril 20 mg/ml (N=29) | 4 mg – One Nasal Spray in one nostril 40 mg/ml (N=29) | 8 mg –Two Nasal Sprays, one in each nostril 40 mg/ml (N=29) | 0.4 mg Intramuscular Injection (N=29)
tmax(h) [t max reported as median (minimum, maximum)] | 0.33 (0.25, 1.00) | 0.33 (0.17, 0.57) | 0.50 (0.17, 1.00) | 0.33 (0.17, 1.00) | 0.38 (0.08, 2.05)
Cmax(ng/mL) | 2.91 (35) | 6.30 (34) | 4.83 (43) | 9.70 (36) | 0.88 (31)
AUCt (hr.ng/mL) | 4.60 (27) | 9.64 (24) | 7.87 (37) | 15.3 (23) | 1.75 (23)
AUC0-inf(h*ng/mL) | 4.66 (27) | 9.74 (24) | 7.95 (37) | 15.5 (23) | 1.79 (23)
t½ (h) | 1.85 (33) | 2.19 (33) | 2.08 (30) | 2.10 (32) | 1.24 (26)
Dose normalized Relative BA (%) vs. IM | 51.7 (22) | 54.0 (23) | 44.2 (31) [N=28 for Relative BA.] | 43.1 (24) | 100

Figure 1 Mean ± SD Plasma Concentration of Naloxone, (a) 0-6 h and (b) 0-1h Following Intranasal Administration and Intramuscular Injection

(a)

(b)

The median naloxone tmaxafter intranasal administration of NARCAN Nasal Spray (one nasal spray in one nostril (2 mg or 4 mg) or two nasal sprays as one spray in each nostril (4 mg or 8 mg) was not significantly different compared to the 0.4 mg dose of naloxone hydrochloride intramuscular injection (Table 1).

The dose normalized relative bioavailability of one dose (2 mg or 4 mg) or two doses (4 mg or 8 mg) of NARCAN Nasal Spray as compared to the 0.4 mg dose of naloxone hydrochloride administered by intramuscular injection was 52%, 44%, 54%, and 43%, respectively.

Distribution

Following parenteral administration, naloxone is distributed in the body and readily crosses the placenta. Plasma protein binding occurs but is relatively weak. Plasma albumin is the major binding constituent, but significant binding of naloxone also occurs to plasma constituents other than albumin. It is not known whether naloxone is excreted into human milk.

Elimination

Following a single intranasal administration of NARCAN Nasal Spray (2 mg or 4 mg dose of naloxone hydrochloride), the mean plasma half-life of naloxone in healthy adults was approximately 1.85 (33% CV) hours and 2.08 (30% CV) hours; respectively, which was longer than that observed after administrations of a 0.4 mg naloxone hydrochloride intramuscular injection, where the half-life was 1.24 hours (26% CV). In a neonatal study of naloxone hydrochloride injection, the mean (± SD) plasma half-life was observed to be 3.1 (± 0.5) hours.

13 NONCLINICAL TOXICOLOGY

13.1 Carcinogenesis, Mutagenesis, Impairment of Fertility

Carcinogenesis

Long-term animal studies to evaluate the carcinogenic potential of naloxone have not been completed.

Mutagenesis

Naloxone was weakly positive in the Ames mutagenicity and in the in vitro human lymphocyte chromosome aberration test but was negative in the in vitro Chinese hamster V79 cell HGPRT mutagenicity assay and in the in vivo rat bone marrow chromosome aberration study.

Impairment of Fertility

Male rats were treated with 2 or 10 mg/kg naloxone for 60 days prior to mating. Female rats treated for 14-days prior to mating and throughout gestation with the same doses of naloxone (up to 12-times a human dose of 8 mg/day (two NARCAN Nasal Sprays) based on body surface area comparison). There was no adverse effect on fertility.

16 HOW SUPPLIED/STORAGE AND HANDLING

16.1 How Supplied

NARCAN Nasal Spray 4 mg is supplied as Carton containing two (2) blister packages (NDC 69547-353-02) each with a single spray device.

NARCAN Nasal Spray is not made with natural rubber latex.

16.2 Storage and Handling

Store NARCAN Nasal Spray in the blister and cartons provided.

Store below 77°F (25°C). Excursions permitted up to 104°F (40°C). Do not freeze or expose to excessive heat above 104°F (40°C). Protect from light.

NARCAN Nasal Spray freezes at temperatures below 5°F (-15°C). If this happens, the device will not spray. If NARCAN Nasal Spray is frozen and is needed in an emergency, do NOT wait for NARCAN Nasal Spray to thaw. Get emergency medical help right away. However, NARCAN Nasal Spray may be thawed by allowing it to sit at room temperature for 15 minutes, and it may still be used if it has been thawed after being previously frozen.

17 PATIENT COUNSELING INFORMATION

Advise the patient and family members or caregivers to read the FDA-approved patient labeling (Patient Informationand Instructions for Use).

Recognition of Opioid Overdose

Inform patients and their family members or caregivers about how to recognize the signs and symptoms of an opioid overdose such as the following:

- Extreme somnolence - inability to awaken a patient verbally or upon a firm sternal rub.
- Respiratory depression - this can range from slow or shallow respiration to no respiration in a patient who is unarousable.
- Other signs and symptoms that may accompany somnolence and respiratory depression include the following:
  - Miosis.
  - Bradycardia and/or hypotension.

Risk of Recurrent Respiratory and Central Nervous System Depression

Instruct patients and their family members or caregivers that, since the duration of action of most opioids may exceed that of NARCAN Nasal Spray, they must seek immediate emergency medical assistance after the first dose of NARCAN Nasal Spray and keep the patient under continued surveillance [see Dosage and Administration (2.2), Warnings and Precautions (5.3)] .

Limited Efficacy for/with Partial Agonists or Mixed Agonist/Antagonists

Instruct patients and their family members or caregivers that the reversal of respiratory depression caused by partial agonists or mixed agonist/antagonists, such as buprenorphine and pentazocine, may be incomplete and may require higher doses of naloxone hydrochloride or repeated administration of NARCAN Nasal Spray, using a new nasal spray each time [see Dosage and Administration (2.3), Warnings and Precautions (5.2)] .

Precipitation of Severe Opioid Withdrawal

Instruct patients and their family members or caregivers that the use of NARCAN Nasal Spray in patients who are opioid dependent may precipitate opioid withdrawal [see Warnings and Precautions (5.3), Adverse Reactions (6)] .

Administration Instructions

Instruct patients and their family members or caregivers to:

- Ensure NARCAN Nasal Spray is present whenever persons may be intentionally or accidentally exposed to an opioid overdose (i.e., opioid emergencies).
- Administer NARCAN Nasal Spray as quickly as possible if a patient is unresponsive and an opioid overdose is suspected, even when in doubt, because prolonged respiratory depression may result in damage to the central nervous system or death. NARCAN Nasal Spray is not a substitute for emergency medical care [see Dosage and Administration (2.1)] .
- Lay the patient on their back and administer NARCAN Nasal Spray into one nostril while providing support to the back of the neck to allow the head to tilt back [see Dosage and Administration (2.1)] .
- Use each nasal spray only one time [see Dosage and Administration (2.1)] .
- Turn patient on their side as shown in the Instructions for Useand call for emergency medical assistance immediately after administration of the first dose of NARCAN Nasal Spray. Additional supportive and/or resuscitative measures may be helpful while awaiting emergency medical assistance [see Dosage and Administration (2.1)].
- Monitor patients and re-administer NARCAN Nasal Spray using a new NARCAN Nasal Spray every 2 to 3 minutes, if the patient is not responding or responds and then relapses back into respiratory depression. Administer NARCAN Nasal Spray in alternate nostrils with each dose [see Dosage and Administration (2.1)] .
- Replace NARCAN Nasal Spray before its expiration date.

NARCAN®is a registered trademark licensed by Emergent Operations Ireland Limited.

Distributed by Emergent Devices Inc., Plymouth Meeting, PA 19462 USA.

PATIENT INFORMATION
NARCAN (nar´ kan)
(naloxone hydrochloride)
Nasal Spray

You and your family members or caregivers should read this Patient Information leaflet before an opioid emergency happens. This information does not take the place of talking with your healthcare provider about your medical condition or your treatment.

What is the most important information I should know about NARCAN Nasal Spray?
NARCAN Nasal Spray is used to temporarily reverse the effects of opioid medicines. The medicine in NARCAN Nasal Spray has no effect in people who are not taking opioid medicines. Always carry NARCAN Nasal Spray with you in case of an opioid emergency.

1. Use NARCAN Nasal Spray right away if you or your caregiver think signs or symptoms of an opioid emergency are present, even if you are not sure, because an opioid emergency can cause severe injury or death. Signs and symptoms of an opioid emergency may include:
  1. unusual sleepiness and you are not able to awaken the person with a loud voice or by rubbing firmly on the middle of their chest (sternum)
  2. breathing problems including slow or shallow breathing in someone difficult to awaken or who looks like they are not breathing
  3. the black circle in the center of the colored part of the eye (pupil) is very small, sometimes called "pinpoint pupils," in someone difficult to awaken
2. Family members, caregivers, or other people who may have to use NARCAN Nasal Spray in an opioid emergency should know where NARCAN Nasal Spray is stored and how to give NARCAN before an opioid emergency happens.
3. Get emergency medical help right away after giving the first dose of NARCAN Nasal Spray.Rescue breathing or CPR (cardiopulmonary resuscitation) may be given while waiting for emergency medical help.
4. The signs and symptoms of an opioid emergency can return after NARCAN Nasal Spray is given. If this happens, give another dose after 2 to 3 minutes using a new NARCAN Nasal Spray and watch the person closely until emergency help is received.

What is NARCAN Nasal Spray?

- NARCAN Nasal Spray is a prescription medicine used for the treatment of an opioid emergency such as an overdose or a possible opioid overdose with signs of breathing problems and severe sleepiness or not being able to respond.
- NARCAN Nasal Spray is to be given right away and does not take the place of emergency medical care. Get emergency medical help right away after giving the first dose of NARCAN Nasal Spray, even if the person wakes up.
- NARCAN Nasal Spray is safe and effective in children for known or suspected opioid overdose.

Who should not use NARCAN Nasal Spray?
Do not use NARCAN Nasal Sprayif you are allergic to naloxone hydrochloride or any of the ingredients in NARCAN Nasal Spray. See the end of this leaflet for a complete list of ingredients in NARCAN Nasal Spray.

What should I tell my healthcare provider before using NARCAN Nasal Spray?
Before using NARCAN Nasal Spray, tell your healthcare provider about all of your medical conditions, including if you:

- have heart problems
- are pregnant or plan to become pregnant. Use of NARCAN Nasal Spray may cause withdrawal symptoms in your unborn baby. Your unborn baby should be examined by a healthcare provider right away after you use NARCAN Nasal Spray.
- are breastfeeding or plan to breastfeed. It is not known if NARCAN Nasal Spray passes into your breast milk.

Tell your healthcare provider about the medicines you take,including prescription and over-the-counter medicines, vitamins, and herbal supplements.

How should I use NARCAN Nasal Spray?
Read the "Instructions for Use" at the end of this Patient Information leaflet for detailed information about the right way to use NARCAN Nasal Spray.

- Use NARCAN Nasal Spray exactly as prescribed by your healthcare provider.
- Each NARCAN Nasal Spray contains only 1 dose of medicine and cannot be reused.
- NARCAN Nasal Spray comes in a 4 mg strength. Your healthcare provider will prescribe the one that is right for you.
- Lay the person on their back. Support their neck with your hand and allow the head to tilt back before giving NARCAN Nasal Spray.
- NARCAN Nasal Spray should be given into one nostril.
- If additional doses are needed, give NARCAN Nasal Spray in the other nostril.

What are the possible side effects of NARCAN Nasal Spray?
NARCAN Nasal Spray may cause serious side effects, including:

- Sudden opioid withdrawal symptoms.In someone who has been using opioids regularly, opioid withdrawal symptoms can happen suddenly after receiving NARCAN Nasal Spray and may include:

- body aches
- diarrhea
- increased heart rate
- fever
- runny nose

- sneezing
- goose bumps
- sweating
- yawning
- nausea or vomiting

- nervousness
- restlessness or irritability
- shivering or trembling
- stomach cramping
- weakness
- increased blood pressure

In infants under 4 weeks old who have been receiving opioids regularly, sudden opioid withdrawal may be life-threatening if not treated the right way. Signs and symptoms include: seizures, crying more than usual, and increased reflexes.
These are not all of the possible side effects of NARCAN Nasal Spray. Call your doctor for medical advice about side effects. You may report side effects to FDA at 1-800-FDA-1088.

How should I store NARCAN Nasal Spray?

- Store below 77°F (25°C).
- Excursions permitted up to 104°F (40°C).
- Do not freeze or expose to excessive heat above 104°F (40°C).'
- Keep NARCAN Nasal Spray in its box until ready to use. Protect from light.
- Replace NARCAN Nasal Spray before the expiration date on the box.

Keep NARCAN Nasal Spray and all medicines out of the reach of children.

General information about the safe and effective use of NARCAN Nasal Spray.
Medicines are sometimes prescribed for purposes other than those listed in a Patient Information leaflet. Do not use NARCAN Nasal Spray for a condition for which it was not prescribed. You can ask your pharmacist or healthcare provider for information about NARCAN Nasal Spray that is written for health professionals.

What are the ingredients in NARCAN Nasal Spray?
Active ingredient:naloxone hydrochloride
Inactive ingredients:benzalkonium chloride (preservative), disodium ethylenediaminetetraacetate (stabilizer), sodium chloride, hydrochloric acid to adjust pH and sterile water
NARCAN Nasal Spray is not made with natural rubber latex.
Distributed by Emergent Devices Inc., Plymouth Meeting, PA 19462 USA.
For more information, go to www.narcan.comor call 1-844-4NARCAN (1-844-462-7226).

This Patient Information has been approved by the U.S. Food and Drug Administration.
Issued: xx/202X

Instructions for Use NARCAN (nar´ kan) (naloxone hydrochloride) Nasal Spray

You and your family members or caregivers should read the Instructions for Use that comes with NARCAN Nasal Spray before using it. Talk to your healthcare provider if you and your family members or caregivers have any questions about the use of NARCAN Nasal Spray.

Use NARCAN Nasal Spray for known or suspected opioid overdose in adults and children.

Important: For use in the nose only.

- Do not remove or test the NARCAN Nasal Spray until ready to use.
- Each NARCAN Nasal Spray has 1 dose and cannot be reused.
- You do not need to prime NARCAN Nasal Spray.

How to use NARCAN Nasal Spray:

Step 1. | Lay the person on their back to receive a dose of NARCAN Nasal Spray.
Step 2. | Remove NARCAN Nasal Spray from the box. Peel back the tab with the circle to open the NARCAN Nasal Spray.
Note:NARCAN Nasal Spray freezes at temperatures below 5°F (-15°C). If this happens, the device will not spray. Get emergency medical help right away if this happens. Do not wait for NARCAN Nasal Spray to thaw. NARCAN Nasal Spray may still be used if it has been thawed after being previously frozen.
Step 3. | Hold the NARCAN Nasal Spray with your thumb on the bottom of the red plunger and your first and middle fingers on either side of the nozzle.
Step 4. | Tilt the person's head back and provide support under the neck with your hand. Gently insert the tip of the nozzle into one nostriluntil your fingers on either side of the nozzle are against the bottom of the person's nose.
Step 5. | Press the red plunger firmly to give the dose of NARCAN Nasal Spray.
Step 6. | Remove the NARCAN Nasal Spray from the nostril after giving the dose.

What to do after NARCAN Nasal Spray has been used:

Step 7. | Get emergency medical help right away.
- Move the person on their side (recovery position) after giving NARCAN Nasal Spray. - Watch the person closely. - If the person does not respond by waking up, to voice or touch, or breathing normally another dose may be given. NARCAN Nasal Spray may be dosed every 2 to 3 minutes, if available.
- Repeat Steps 2 through 6using a new NARCAN Nasal Spray to give another dose in the other nostril. If additional NARCAN Nasal Sprays are available, Steps 2 through 6 may be repeated every 2 to 3 minutes until the person responds or emergency medical help is received.
Step 8. | Put the used NARCAN Nasal Spray back into its box.
Step 9. | Throw away (dispose of) the used NARCAN Nasal Spray in a place that is away from children.

How should I store NARCAN Nasal Spray?

- Store below 77°F (25°C).
- Excursions permitted up to 104°F (40°C).
- Do not freeze or expose to excessive heat above 104°F (40°C).
- Keep NARCAN Nasal Spray in the box until ready to use. Protect from light.
- Replace NARCAN Nasal Spray before the expiration date on the box.

Keep NARCAN Nasal Spray and all medicines out of the reach of children.

This Instructions for Use has been approved by the U.S. Food and Drug Administration.

Distributed by Emergent Devices Inc. Plymouth Meeting, PA 19462 USA.

For more information, go to www.narcan.comor call 1-844-4NARCAN (1-844-462-7226).

Issued: 11/2020

PRINCIPAL DISPLAY PANEL - 4 mg Vial Package

NDC 69547-353-02
0.1 mL intranasal spray per unit
For use in the nose only
Rx Only

NARCAN®(naloxone HCl)
NASAL SPRAY 4 mg

Use NARCAN®Nasal Spray for known or suspected
opioid overdose in adults and children.

Important: For use in the nose only.

Do not remove or test the NARCAN®Nasal Spray
until ready to use

This box contains two (2) 4-mg doses of naloxone
HCl nasal spray

Two Pack

CHECK PRODUCT EXPIRATION DATE BEFORE USE.

OPEN HERE FOR QUICK START GUIDE
Opioid Overdose Response Instructions

PRINCIPAL DISPLAY PANEL - 4 mg Vial Package

For use in the nose only
NDC 69547-353-02

Rx Only

NARCAN®(naloxone HCl)
NASAL SPRAY 4 mg

1 spray per device

Each dose contains 4 mg naloxone HCl
(equivalent to 3.6 mg naloxone) in 0.1 mL nasal spray
Store below 77°F (25°C).
Excursions permitted up to 104°F (40°C).
Do not freeze or expose to excessive heat
above 104°F (40°C). Protect from light.
Use for known or suspected opioid overdose
in adults and children
SEE ENCLOSED QUICK START GUIDE

LOT_XXXXXX_EXP_MMM_YYYY

Distributed by Emergent Devices Inc.
Plymouth Meeting, PA 19462 USA

DO NOT TEST DEVICE BEFORE USE